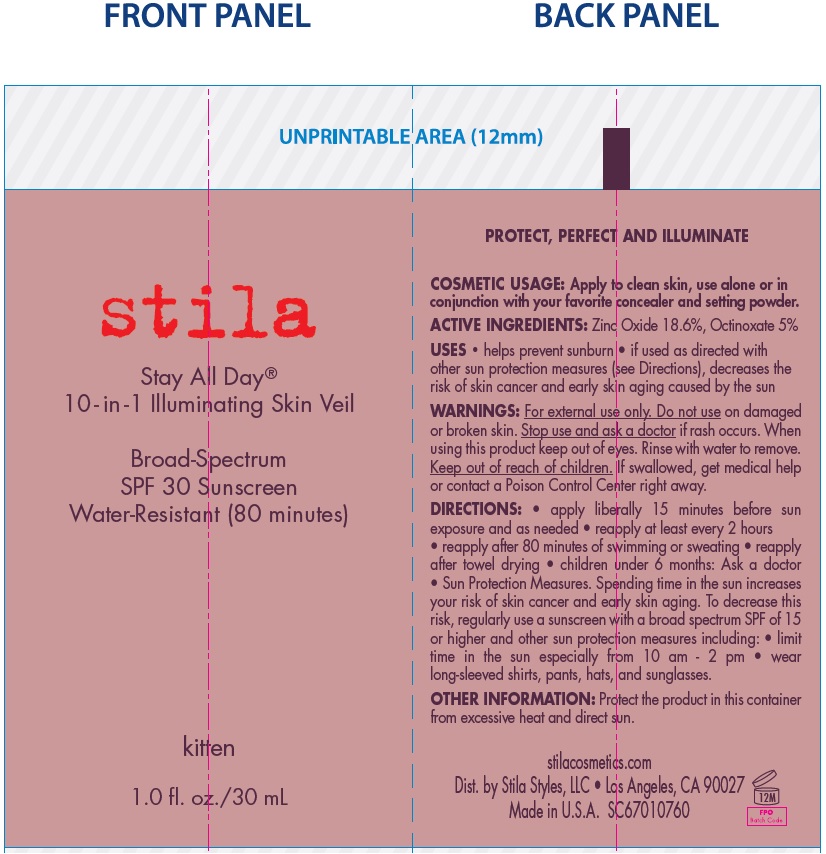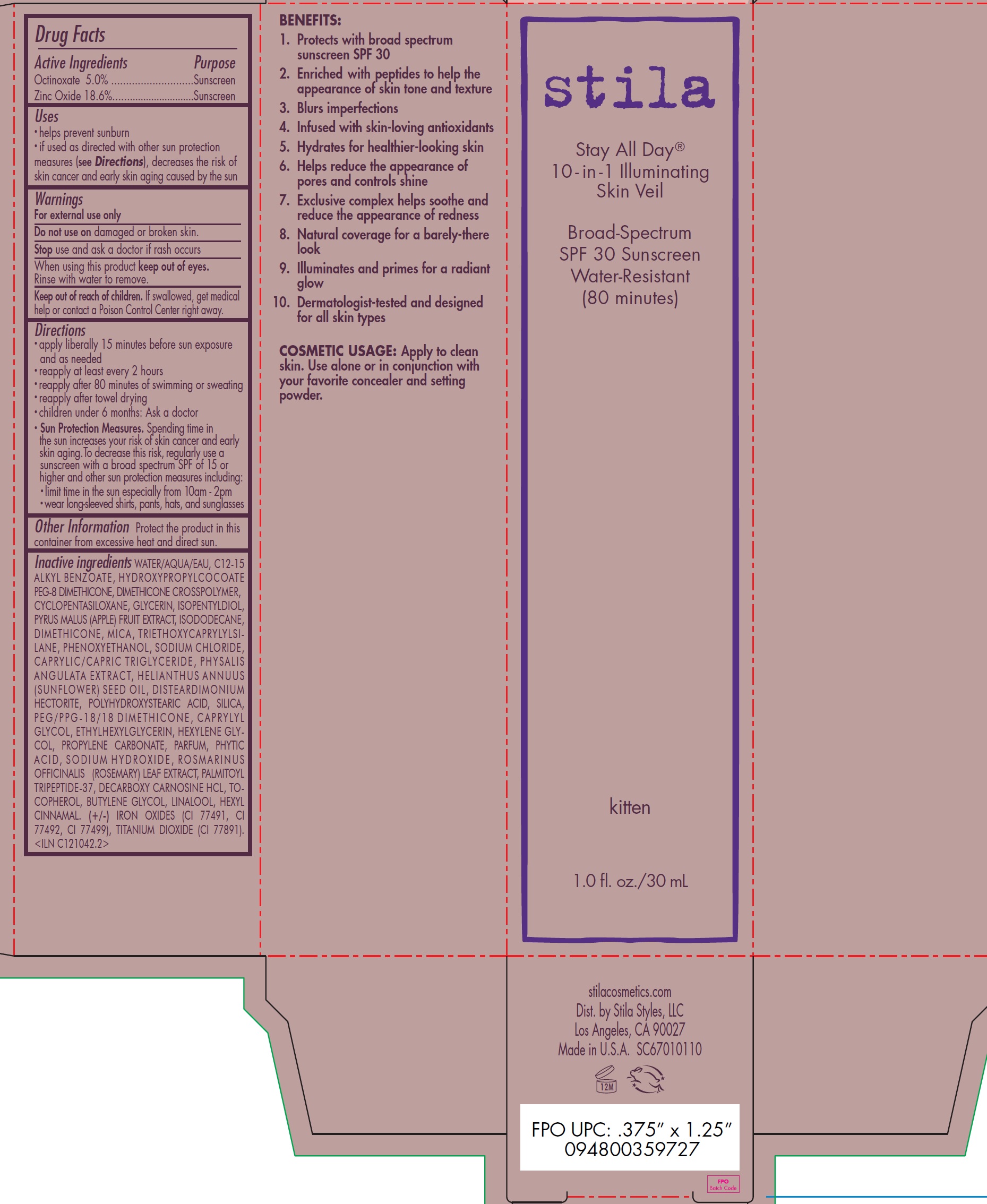 DRUG LABEL: Stay All Day 10-in-1 Illuminating Skin Veil Broad-Spectrum SPF 30 Sunscreen Water-Resistant 80 minutes KITTEN
NDC: 76049-202 | Form: CREAM
Manufacturer: Stila Style, LLC
Category: otc | Type: HUMAN OTC DRUG LABEL
Date: 20220411

ACTIVE INGREDIENTS: OCTINOXATE 50 mg/1 mL; ZINC OXIDE 186 mg/1 mL
INACTIVE INGREDIENTS: WATER; ALKYL (C12-15) BENZOATE; HYDROXYPROPYLCOCOATE PEG-8 DIMETHICONE; CYCLOMETHICONE 5; GLYCERIN; ISOPENTYLDIOL; APPLE; ISODODECANE; DIMETHICONE; MICA; TRIETHOXYCAPRYLYLSILANE; PHENOXYETHANOL; SODIUM CHLORIDE; MEDIUM-CHAIN TRIGLYCERIDES; PHYSALIS ANGULATA WHOLE; SUNFLOWER OIL; DISTEARDIMONIUM HECTORITE; SILICON DIOXIDE; PEG/PPG-18/18 DIMETHICONE; CAPRYLYL GLYCOL; ETHYLHEXYLGLYCERIN; HEXYLENE GLYCOL; PROPYLENE CARBONATE; FYTIC ACID; SODIUM HYDROXIDE; ROSEMARY; DECARBOXY CARNOSINE HYDROCHLORIDE; TOCOPHEROL; BUTYLENE GLYCOL; LINALOOL, (+/-)-; CINNAMALDEHYDE; FERRIC OXIDE RED; FERRIC OXIDE YELLOW; FERROSOFERRIC OXIDE

Stay All Day® 10-in-1 Illuminating Skin Veil Broad-Spectrum SPF 30 Sunscreen Water-Resistant (80 minutes) KITTEN

Active Ingredients

Octinoxate 5.0%

Zinc Oxide 18.6%

Purpose

Sunscreen

Uses

• helps prevent sunburn
• if used as directed with other sun protection measures (see Directions), decreases the risk of skin cancer and early skin aging caused by the sun

Warnings

For external use only

Do not use

on damaged or broken skin.

Stop use and ask a doctor

if rash occurs.

When using this product

keep out of eyes. Rinse with water to remove.

Keep out of reach of children.

If swallowed, get medical help or contact a Poison Control Center right away.

Directions

• apply liberally 15 minutes before sun exposure and as needed
• reapply at least every 2 hours
• reapply after 80 minutes of swimming or sweating
• reapply after towel drying
• children under 6 months: Ask a doctor
• Sun Protection Measures. Spending time in the sun increases your risk of skin cancer and early skin aging.To decrease this risk, regularly use a sunscreen with a broad spectrum SPF of 15 or higher and other sun protection measures including:
• limit time in the sun especially from 10am - 2pm
• wear long-sleeved shirts, pants, hats, and sunglasses

Other Information

Protect the product in this container from excessive heat and direct sun.

Inactive ingredients :

WATER/AQUA/EAU, C12-15 ALKYL BENZOATE, HYDROXYPROPYLCOCOATE PEG-8 DIMETHICONE, DIMETHICONE CROSSPOLYMER,-
CYCLOPENTASILOXANE, GLYCERIN, ISOPENTYLDIOL, PYRUS MALUS (APPLE) FRUIT EXTRACT, ISODODECANE, DIMETHICONE, MICA, TRIETHOXYCAPRYLYLSILANE, PHENOXYETHANOL, SODIUM CHLORIDE, CAPRYLIC/CAPRIC TRIGLYCERIDE, PHYSALIS ANGULATA EXTRACT, HELIANTHUS ANNUUS (SUNFLOWER) SEED OIL, DISTEARDIMONIUM HECTORITE, POLYHYDROXYSTEARIC ACID, SILICA, PEG/PPG-18/18 DIMETHICONE, CAPRYLYL GLYCOL, ETHYLHEXYLGLYCERIN, HEXYLENE GLYCOL, PROPYLENE CARBONATE, PARFUM, PHYTIC ACID, SODIUM HYDROXIDE, ROSMA R INUS OFFICINALIS (ROSEMARY) LEAF EXTRACT, PALMITOYL TRIPEPTIDE-37, DECARBOXY CARNOSINE HCL, TOCOPHEROL, BUTYLENE GLYCOL, LINALOOL, HEXYL CINNAMAL. (+/-) IRON OXIDES (CI 77491, CI 77492, CI 77499), TITANIUM DIOXIDE (CI 77891). <ILN C121042.2>